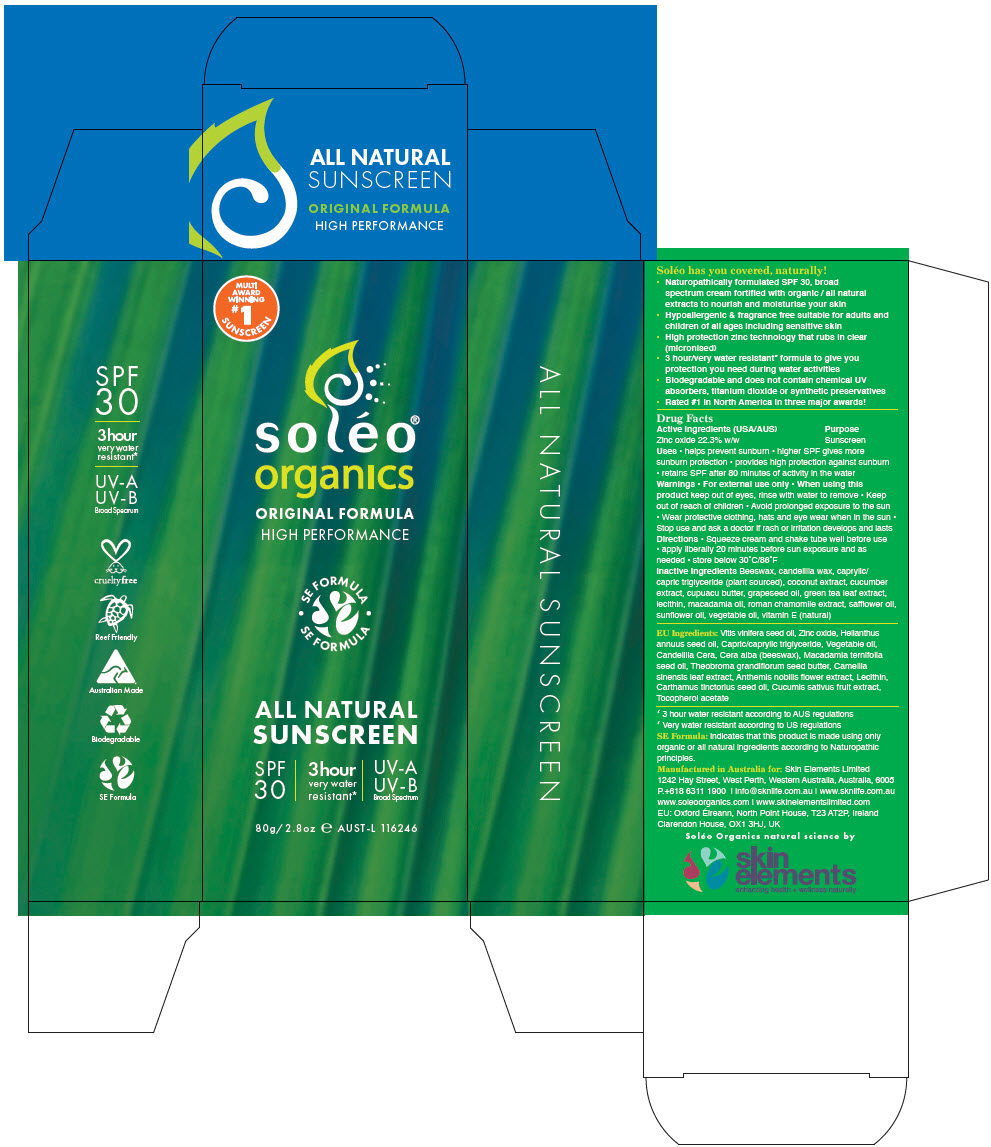 DRUG LABEL: Soleo Organics Sunscreen
NDC: 11045-0303 | Form: CREAM
Manufacturer: SE Operations Pty Ltd
Category: otc | Type: HUMAN OTC DRUG LABEL
Date: 20250122

ACTIVE INGREDIENTS: Zinc Oxide 223 mg/1 g
INACTIVE INGREDIENTS: GRAPE SEED OIL; SUNFLOWER OIL; MEDIUM-CHAIN TRIGLYCERIDES; CANDELILLA WAX; YELLOW WAX; MACADAMIA OIL; THEOBROMA GRANDIFLORUM SEED BUTTER; GREEN TEA LEAF; CHAMAEMELUM NOBILE FLOWER; SOYBEAN LECITHIN; SAFFLOWER OIL; CUCUMBER; .ALPHA.-TOCOPHEROL

Soléo® Organics

Drug Facts

Active Ingredients (USA/AUS)

Zinc oxide 22.3% w/w

Purpose

Sunscreen

Uses

- helps prevent sunburn
- higher SPF gives more sunburn protection
- provides high protection against sunburn
- retains SPF after 80 minutes of activity in the water

Warnings

- For external use only

- When using this product keep out of eyes, rinse with water to remove

- Keep out of reach of children

- Avoid prolonged exposure to the sun
- Wear protective clothing, hats and eye wear when in the sun
- Stop use and ask a doctor if rash or irritation develops and lasts

Directions

- Squeeze cream and shake tube well before use
- apply liberally 20 minutes before sun exposure and as needed
- store below 30°C/86°F

Inactive Ingredients

Beeswax, candelilla wax, caprylic/capric triglyceride (plant sourced), coconut extract, cucumber extract, cupuacu butter, grapeseed oil, green tea leaf extract, lecithin, macadamia oil, roman chamomile extract, safflower oil, sunflower oil, vegetable oil, vitamin E (natural)

PRINCIPAL DISPLAY PANEL - 80 g Tube Carton

MULTI
AWARD
WINNING
#1
SUNSCREEN

soléo®
organics

ORIGINAL FORMULA
HIGH PERFORMANCE

• SE FORMULA •
SE FORMULA

ALL NATURAL
SUNSCREEN

SPF
30

3hour
very water
resistant*

UV-A
UV-B
Broad Spectrum

80g/2.8 oz e AUST-L 116246